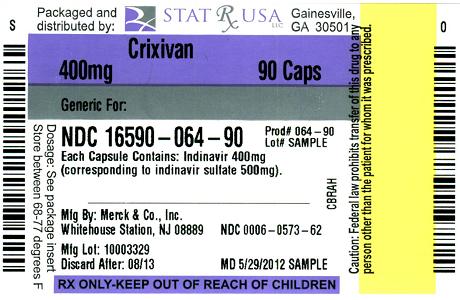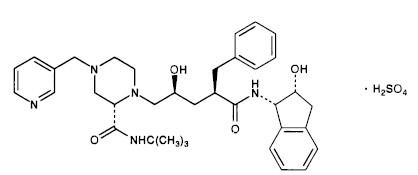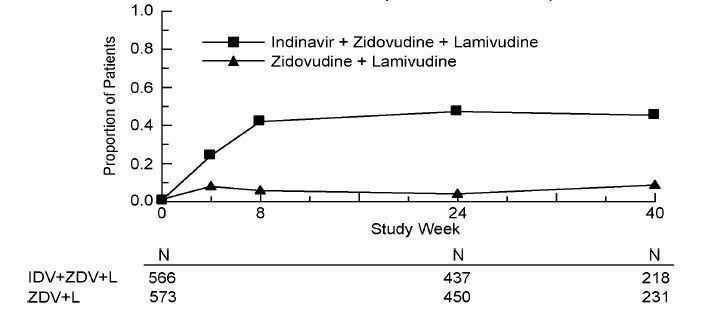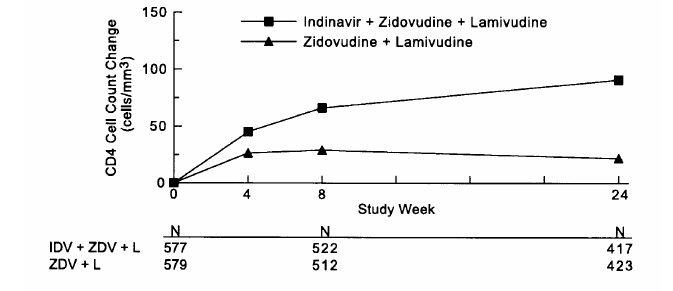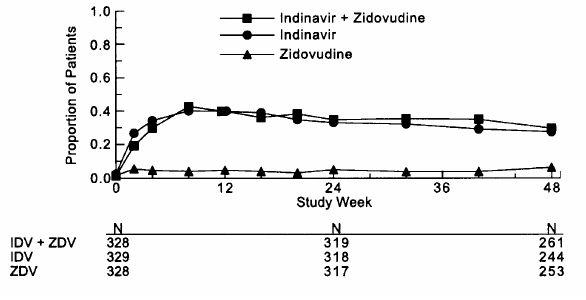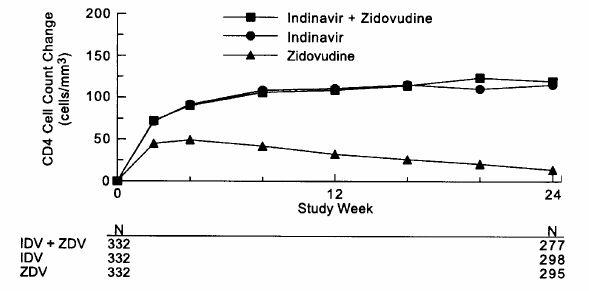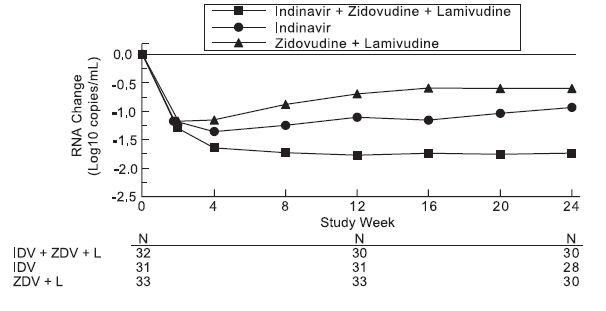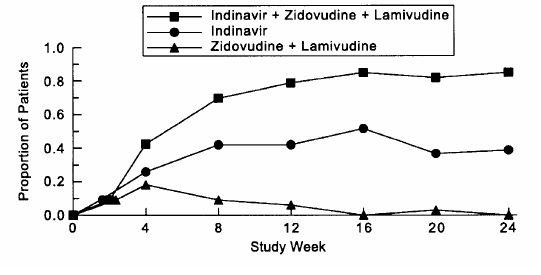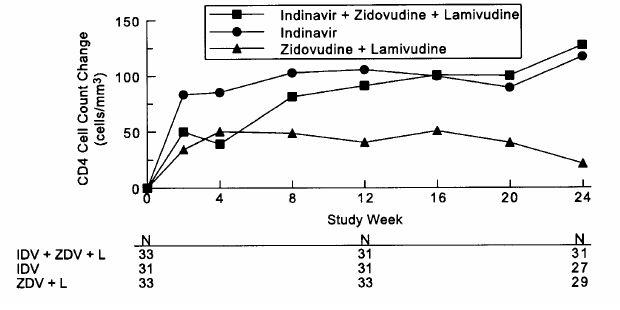 DRUG LABEL: CRIXIVAN
NDC: 16590-064 | Form: CAPSULE
Manufacturer: STAT Rx USA LLC
Category: prescription | Type: HUMAN PRESCRIPTION DRUG LABEL
Date: 20120614

ACTIVE INGREDIENTS: INDINAVIR SULFATE 400 mg/1 1
INACTIVE INGREDIENTS: ANHYDROUS LACTOSE; MAGNESIUM STEARATE; GELATIN; TITANIUM DIOXIDE

CRIXIVAN®
(INDINAVIR SULFATE)
CAPSULES

DESCRIPTION

CRIXIVAN® (indinavir sulfate) is an inhibitor of the human immunodeficiency virus (HIV) protease. CRIXIVAN Capsules are formulated as a sulfate salt and are available for oral administration in strengths of 100, 200, and 400 mg of indinavir (corresponding to 125, 250, and 500 mg indinavir sulfate, respectively). Each capsule also contains the inactive ingredients anhydrous lactose and magnesium stearate. The capsule shell has the following inactive ingredients and dyes: gelatin and titanium dioxide.

The chemical name for indinavir sulfate is [1(1S,2R),5(S)]-2,3,5-trideoxy-N-(2,3-dihydro-2-hydroxy-1H-inden-1-yl)-5-[2-[[(1,1-dimethylethyl)amino]carbonyl]-4-(3-pyridinylmethyl)-1-piperazinyl]-2-(phenylmethyl)-D-erythro-pentonamide sulfate (1:1) salt. Indinavir sulfate has the following structural formula:

Indinavir sulfate is a white to off-white, hygroscopic, crystalline powder with the molecular formula C36H47N5O4 • H2SO4 and a molecular weight of 711.88. It is very soluble in water and in methanol.

MICROBIOLOGY

Mechanism of Action:

HIV-1 protease is an enzyme required for the proteolytic cleavage of the viral polyprotein precursors into the individual functional proteins found in infectious HIV-1. Indinavir binds to the protease active site and inhibits the activity of the enzyme. This inhibition prevents cleavage of the viral polyproteins resulting in the formation of immature non-infectious viral particles.

Antiretroviral Activity In Vitro:

The in vitro activity of indinavir was assessed in cell lines of lymphoblastic and monocytic origin and in peripheral blood lymphocytes. HIV-1 variants used to infect the different cell types include laboratory-adapted variants, primary clinical isolates and clinical isolates resistant to nucleoside analogue and nonnucleoside inhibitors of the HIV-1 reverse transcriptase. The IC95 (95% inhibitory concentration) of indinavir in these test systems was in the range of 25 to 100 nM. In drug combination studies with the nucleoside analogues zidovudine and didanosine, indinavir showed synergistic activity in cell culture. The relationship between in vitro susceptibility of HIV-1 to indinavir and inhibition of HIV-1 replication in humans has not been established.

Drug Resistance:

Isolates of HIV-1 with reduced susceptibility to the drug have been recovered from some patients treated with indinavir. Viral resistance was correlated with the accumulation of mutations that resulted in the expression of amino acid substitutions in the viral protease. Eleven amino acid residue positions, (L10l/V/R, K20l/M/R, L24l, M46l/L, l54A/V, L63P, l64V, A71T/V, V82A/F/T, l84V, and L90M), at which substitutions are associated with resistance, have been identified. Resistance was mediated by the co-expression of multiple and variable substitutions at these positions. No single substitution was either necessary or sufficient for measurable resistance (≥4-fold increase in IC95). In general, higher levels of resistance were associated with the co-expression of greater numbers of substitutions, although their individual effects varied and were not additive. At least 3 amino acid substitutions must be present for phenotypic resistance to indinavir to reach measurable levels. In addition, mutations in the p7/ p1 and p1/ p6 gag cleavage sites were observed in some indinavir resistant HIV-1 isolates.

In vitro phenotypic susceptibilities to indinavir were determined for 38 viral isolates from 13 patients who experienced virologic rebounds during indinavir monotherapy. Pre-treatment isolates from five patients exhibited indinavir IC95 values of 50-100 nM. At or following viral RNA rebound (after 12-76 weeks of therapy), IC95 values ranged from 25 to >3000 nM, and the viruses carried 2 to 10 mutations in the protease gene relative to baseline.

Cross-Resistance to Other Antiviral Agents:

Varying degrees of HIV-1 cross-resistance have been observed between indinavir and other HIV-1 protease inhibitors. In studies with ritonavir, saquinavir, and amprenavir, the extent and spectrum of cross-resistance varied with the specific mutational patterns observed. In general, the degree of cross-resistance increased with the accumulation of resistance-associated amino acid substitutions. Within a panel of 29 viral isolates from indinavir-treated patients that exhibited measurable (≥4-fold) phenotypic resistance to indinavir, all were resistant to ritonavir. Of the indinavir resistant HIV-1 isolates, 63% showed resistance to saquinavir and 81% to amprenavir.

CLINICAL PHARMACOLOGY

Pharmacokinetics

Absorption:

Indinavir was rapidly absorbed in the fasted state with a time to peak plasma concentration (Tmax) of 0.8 ± 0.3 hours (mean ± S.D.) (n=11). A greater than dose-proportional increase in indinavir plasma concentrations was observed over the 200-1000 mg dose range. At a dosing regimen of 800 mg every 8 hours, steady-state area under the plasma concentration time curve (AUC) was 30,691 ± 11,407 nM•hour (n=16), peak plasma concentration (Cmax) was 12,617 ± 4037 nM (n=16), and plasma concentration eight hours post dose (trough) was 251 ± 178 nM (n=16).

Effect of Food on Oral Absorption:

Administration of indinavir with a meal high in calories, fat, and protein (784 kcal, 48.6 g fat, 31.3 g protein) resulted in a 77% ± 8% reduction in AUC and an 84% ± 7% reduction in Cmax (n=10). Administration with lighter meals (e.g., a meal of dry toast with jelly, apple juice, and coffee with skim milk and sugar or a meal of corn flakes, skim milk and sugar) resulted in little or no change in AUC, Cmax or trough concentration.

Distribution:

Indinavir was approximately 60% bound to human plasma proteins over a concentration range of 81 nM to 16,300 nM.

Metabolism:

Following a 400-mg dose of ^14C-indinavir, 83 ± 1% (n=4) and 19 ± 3% (n=6) of the total radioactivity was recovered in feces and urine, respectively; radioactivity due to parent drug in feces and urine was 19.1% and 9.4%, respectively. Seven metabolites have been identified, one glucuronide conjugate and six oxidative metabolites. In vitro studies indicate that cytochrome P-450 3A4 (CYP3A4) is the major enzyme responsible for formation of the oxidative metabolites.

Elimination:

Less than 20% of indinavir is excreted unchanged in the urine. Mean urinary excretion of unchanged drug was 10.4 ± 4.9% (n=10) and 12.0 ± 4.9% (n=10) following a single 700-mg and 1000-mg dose, respectively. Indinavir was rapidly eliminated with a half-life of 1.8 ± 0.4 hours (n=10). Significant accumulation was not observed after multiple dosing at 800 mg every 8 hours.

Special Populations

Hepatic Insufficiency:

Patients with mild to moderate hepatic insufficiency and clinical evidence of cirrhosis had evidence of decreased metabolism of indinavir resulting in approximately 60% higher mean AUC following a single 400-mg dose (n=12). The half-life of indinavir increased to 2.8 ± 0.5 hours. Indinavir pharmacokinetics have not been studied in patients with severe hepatic insufficiency (see DOSAGE AND ADMINISTRATION, Hepatic Insufficiency).

Renal Insufficiency:

The pharmacokinetics of indinavir have not been studied in patients with renal insufficiency.

Gender:

The effect of gender on the pharmacokinetics of indinavir was evaluated in 10 HIV seropositive women who received CRIXIVAN 800 mg every 8 hours with zidovudine 200 mg every 8 hours and lamivudine 150 mg twice a day for one week. Indinavir pharmacokinetic parameters in these women were compared to those in HIV seropositive men (pooled historical control data). Differences in indinavir exposure, peak concentrations, and trough concentrations between males and females are shown in Table 1 below:

Table 1
PK Parameter | % change in PK parameter for females relative to males | 90% Confidence Interval
AUC0-8h (nM•hr) | ↓13% | (↓32%, ↑12%)
Cmax (nM) | ↓13% | (↓32%, ↑10%)
C8h (nM) | ↓22% | (↓47%, ↑15%)
↓Indicates a decrease in the PK parameter; ↑indicates an increase in the PK parameter.

The clinical significance of these gender differences in the pharmacokinetics of indinavir is not known.

Race:

Pharmacokinetics of indinavir appear to be comparable in Caucasians and Blacks based on pharmacokinetic studies including 42 Caucasians (26 HIV-positive) and 16 Blacks (4 HIV-positive).

Pediatric:

The optimal dosing regimen for use of indinavir in pediatric patients has not been established. In HIV-infected pediatric patients (age 4-15 years), a dosage regimen of indinavir capsules, 500 mg/m^2 every 8 hours, produced AUC0-8hr of 38,742 ± 24,098 nM•hour (n=34), Cmax of 17,181 ± 9809 nM (n=34), and trough concentrations of 134 ± 91 nM (n=28). The pharmacokinetic profiles of indinavir in pediatric patients were not comparable to profiles previously observed in HIV-infected adults receiving the recommended dose of 800 mg every 8 hours. The AUC and Cmax values were slightly higher and the trough concentrations were considerably lower in pediatric patients. Approximately 50% of the pediatric patients had trough values below 100 nM; whereas, approximately 10% of adult patients had trough levels below 100 nM. The relationship between specific trough values and inhibition of HIV replication has not been established.

Pregnant Patients:

The optimal dosing regimen for use of indinavir in pregnant patients has not been established. A CRIXIVAN dose of 800 mg every 8 hours (with zidovudine 200 mg every 8 hours and lamivudine 150 mg twice a day) has been studied in 16 HIV-infected pregnant patients at 14 to 28 weeks of gestation at enrollment (study PACTG 358). The mean indinavir plasma AUC0-8hr at weeks 30-32 of gestation (n=11) was 9231 nM•hr, which is 74% (95% CI: 50%, 86%) lower than that observed 6 weeks postpartum. Six of these 11 (55%) patients had mean indinavir plasma concentrations 8 hours post-dose (Cmin) below assay threshold of reliable quantification. The pharmacokinetics of indinavir in these 11 patients at 6 weeks postpartum were generally similar to those observed in non-pregnant patients in another study (see PRECAUTIONS, Pregnancy).

Drug Interactions:

(also see CONTRAINDICATIONS, WARNINGS, PRECAUTIONS, Drug Interactions)

Indinavir is an inhibitor of the cytochrome P450 isoform CYP3A4. Coadministration of CRIXIVAN and drugs primarily metabolized by CYP3A4 may result in increased plasma concentrations of the other drug, which could increase or prolong its therapeutic and adverse effects (see CONTRAINDICATIONS and WARNINGS). Based on in vitro data in human liver microsomes, indinavir does not inhibit CYP1A2, CYP2C9, CYP2E1 and CYP2B6. However, indinavir may be a weak inhibitor of CYP2D6.

Indinavir is metabolized by CYP3A4. Drugs that induce CYP3A4 activity would be expected to increase the clearance of indinavir, resulting in lowered plasma concentrations of indinavir. Coadministration of CRIXIVAN and other drugs that inhibit CYP3A4 may decrease the clearance of indinavir and may result in increased plasma concentrations of indinavir.

Drug interaction studies were performed with CRIXIVAN and other drugs likely to be coadministered and some drugs commonly used as probes for pharmacokinetic interactions. The effects of coadministration of CRIXIVAN on the AUC, Cmax and Cmin are summarized in Table 2 (effect of other drugs on indinavir) and Table 3 (effect of indinavir on other drugs). For information regarding clinical recommendations, see Table 9 in PRECAUTIONS.

Table 2: Drug Interactions: Pharmacokinetic Parameters for Indinavir in the Presence of the Coadministered Drug (See PRECAUTIONS, Table 9 for Recommended Alterations in Dose or Regimen)
Coadministered drug | Dose of Coadministered drug (mg) | Dose of CRIXIVAN (mg) | n | Ratio (with/without coadministered drug) of Indinavir Pharmacokinetic Parameters (90% CI); No Effect = 1.00
 |  |  |  | Cmax | AUC | Cmin
Cimetidine | 600 twice daily, 6 days | 400 single dose | 12 | 1.07 (0.77, 1.49) | 0.98 (0.81, 1.19) | 0.82 (0.69, 0.99)
Clarithromycin | 500 q12h, 7 days | 800 three times daily, 7 days | 10 | 1.08 (0.85, 1.38) | 1.19 (1.00, 1.42) | 1.57 (1.16, 2.12)
Delavirdine | 400 three times daily | 400 three times daily, 7 days | 28 | 0.64 [Relative to indinavir 800 mg three times daily alone.] (0.48, 0.86) | No significant change | 2.18 (1.16, 4.12)
Delavirdine | 400 three times daily | 600 three times daily, 7 days | 28 | No significant change | 1.53 (1.07, 2.20) | 3.98 (2.04, 7.78)
Efavirenz [Study conducted in HIV-positive subjects.] | 600 once daily, 10 days | 1000 three times daily, 10 days | 20
 |  | After morning dose |  | No significant change | 0.67 (0.61, 0.74) | 0.61 (0.49, 0.76)
 |  | After afternoon dose |  | No significant change | 0.63 (0.54, 0.74) | 0.48 (0.43, 0.53)
 |  | After evening dose |  | 0.71 (0.57, 0.89) | 0.54 (0.46, 0.63) | 0.43 (0.37, 0.50)
Fluconazole | 400 once daily, 8 days | 1000 three times daily, 7 days | 11 | 0.87 (0.72, 1.05) | 0.76 (0.59, 0.98) | 0.90 (0.72, 1.12)
Grapefruit Juice | 8 oz. | 400 single dose | 10 | 0.65 (0.53, 0.79) | 0.73 (0.60, 0.87) | 0.90 (0.71, 1.15)
Isoniazid | 300 once daily in the morning, 8 days | 800 three times daily, 7 days | 11 | 0.95 (0.88, 1.03) | 0.99 (0.87, 1.13) | 0.89 (0.75, 1.06)
Itraconazole | 200 twice daily, 7 days | 600 three times daily, 7 days | 12 | 0.78 (0.69, 0.88) | 0.99 (0.91, 1.06) | 1.49 (1.28, 1.74)
Ketoconazole | 400 once daily, 7 days | 600 three times daily, 7 days | 12 | 0.69 (0.61, 0.78) | 0.80 (0.74, 0.87) | 1.29 (1.11, 1.51)
 | 400 once daily, 7 days | 400 three times daily, 7 days | 12 | 0.42 (0.37, 0.47) | 0.44 (0.41, 0.48) | 0.73 (0.62, 0.85)
Methadone | 20-60 once daily in the morning, 8 days | 800 three times daily, 8 days | 10 | See text below for discussion of interaction.
Quinidine | 200 single dose | 400 single dose | 10 | 0.96 (0.79, 1.18) | 1.07 (0.89, 1.28) | 0.93 (0.73, 1.19)
Rifabutin | 150 once daily in the morning, 10 days | 800 three times daily, 10 days | 14 | 0.80 (0.72, 0.89) | 0.68 (0.60, 0.76) | 0.60 (0.51, 0.72)
Rifabutin | 300 once daily in the morning, 10 days | 800 three times daily, 10 days | 10 | 0.75 (0.61, 0.91) | 0.66 (0.56, 0.77) | 0.61 (0.50, 0.75)
Rifampin | 600 once daily in the morning, 8 days | 800 three times daily, 7 days | 12 | 0.13 (0.08, 0.22) | 0.08 (0.06, 0.11) | Not Done
Ritonavir | 100 twice daily, 14 days | 800 twice daily, 14 days | 10, 16 [Comparison to historical data on 16 subjects receiving indinavir alone.] | See text below for discussion of interaction.
Ritonavir | 200 twice daily, 14 days | 800 twice daily,14 days | 9, 16 | See text below for discussion of interaction.
Sildenafil | 25 single dose | 800 three times daily | 6 | See text below for discussion of interaction.
St. John's wort (Hypericum perforatum, standardized to 0.3 % hypericin) | 300 three times daily with meals, 14 days | 800 three times daily | 8 | Not Available | 0.46 (0.34, 0.58) [95% CI.] | 0.19 (0.06, 0.33)
Stavudine (d4T) | 40 twice daily, 7 days | 800 three times daily, 7 days | 11 | 0.95 (0.80, 1.11) | 0.95 (0.80, 1.12) | 1.13 (0.83, 1.53)
Trimethoprim/ Sulfamethoxazole | 800 Trimethoprim/ 160 Sulfamethoxazole q12h, 7 days | 400 four times daily, 7 days | 12 | 1.12 (0.87, 1.46) | 0.98 (0.81, 1.18) | 0.83 (0.72, 0.95)
Zidovudine | 200 three times daily, 7 days | 1000 three times daily, 7 days | 12 | 1.06 (0.91, 1.25) | 1.05 (0.86, 1.28) | 1.02 (0.77, 1.35)
Zidovudine/ Lamivudine (3TC) | 200/150 three times daily, 7 days | 800 three times daily, 7 days | 6, 9 [Parallel group design; n for indinavir + coadministered drug, n for indinavir alone.] | 1.05 (0.83, 1.33) | 1.04 (0.67, 1.61) | 0.98 (0.56, 1.73)
All interaction studies conducted in healthy, HIV-negative adult subjects, unless otherwise indicated.

Table 3: Drug Interactions: Pharmacokinetic Parameters for Coadministered Drug in the Presence of Indinavir (See PRECAUTIONS, Table 9 for Recommended Alterations in Dose or Regimen)
Coadministered drug | Dose of Coadministered drug (mg) | Dose of CRIXIVAN (mg) | n | Ratio (with/without CRIXIVAN) of Coadministered Drug Pharmacokinetic Parameters (90% CI); No Effect = 1.00
 |  |  |  | Cmax | AUC | Cmin
Clarithromycin | 500 twice daily, 7 days | 800 three times daily, 7 days | 12 | 1.19 (1.02, 1.39) | 1.47 (1.30, 1.65) | 1.97 (1.58, 2.46) n=11
Efavirenz | 200 once daily, 14 days | 800 three times daily, 14 days | 20 | No significant change | No significant change | --
Ethinyl Estradiol (ORTHO-NOVUM 1/35) [Registered trademark of Ortho Pharmaceutical Corporation.] | 35 mcg, 8 days | 800 three times daily, 8 days | 18 | 1.02 (0.96, 1.09) | 1.22 (1.15, 1.30) | 1.37 (1.24, 1.51)
Isoniazid | 300 once daily in the morning, 8 days | 800 three times daily, 8 days | 11 | 1.34 (1.12, 1.60) | 1.12 (1.03, 1.22) | 1.00 (0.92, 1.08)
Methadone [Study conducted in subjects on methadone maintenance.] | 20-60 once daily in the morning, 8 days | 800 three times daily, 8 days | 12 | 0.93 (0.84, 1.03) | 0.96 (0.86, 1.06) | 1.06 (0.94, 1.19)
Norethindrone (ORTHO-NOVUM 1/35) | 1 mcg, 8 days | 800 three times daily, 8 days | 18 | 1.05 (0.95, 1.16) | 1.26 (1.20, 1.31) | 1.44 (1.32, 1.57)
Rifabutin 150 mg once daily in the morning, 11 days + indinavir compared to 300 mg once daily in the morning, 11 days alone | 150 once daily in the morning, 10 days 300 once daily in the morning, 10 days | 800 three times daily, 10 days 800 three times daily, 10 days | 14 10 | 1.29 (1.05, 1.59) 2.34 (1.64, 3.35) | 1.54 (1.33, 1.79) 2.73 (1.99, 3.77) | 1.99 (1.71, 2.31) n=13 3.44 (2.65, 4.46) n=9
Ritonavir | 100 twice daily, 14 days | 800 twice daily, 14 days | 10, 4 [Parallel group design; n for coadministered drug + indinavir, n for coadministered drug alone.] | 1.61 (1.13, 2.29) | 1.72 (1.20, 2.48) | 1.62 (0.93, 2.85)
 | 200 twice daily, 14 days | 800 twice daily, 14 days | 9, 5 | 1.19 (0.85, 1.66) | 1.96 (1.39, 2.76) | 4.71 (2.66, 8.33) n=9, 4
Saquinavir
Hard gel formulation | 600 single dose | 800 three times daily, 2 days | 6 | 4.7 (2.7, 8.1) | 6.0 (4.0, 9.1) | 2.9 (1.7, 4.7) [C6hr]
Soft gel formulation | 800 single dose | 800 three times daily, 2 days | 6 | 6.5 (4.7, 9.1) | 7.2 (4.3, 11.9) | 5.5 (2.2, 14.1)
Soft gel formulation | 1200 single dose | 800 three times daily, 2 days | 6 | 4.0 (2.7, 5.9) | 4.6 (3.2, 6.7) | 5.5 (3.7, 8.3)
Sildenafil | 25 single dose | 800 three times daily | 6 | See text below for discussion of interaction.
Stavudine [Study conducted in HIV-positive subjects.] | 40 twice daily, 7 days | 800 three times daily, 7 days | 13 | 0.86 (0.73, 1.03) | 1.21 (1.09, 1.33) | Not Done
Theophylline | 250 single dose (on Days 1 and 7) | 800 three times daily, 6 days (Days 2 to 7) | 12, 4 | 0.88 (0.76, 1.03) | 1.14 (1.04, 1.24) | 1.13 (0.86, 1.49) n=7, 3
Trimethoprim/ Sulfamethoxazole
Trimethoprim | 800 Trimethoprim/ 160 Sulfamethoxazole q12h, 7 days | 400 q6h, 7 days | 12 | 1.18 (1.05, 1.32) | 1.18 (1.05, 1.33) | 1.18 (1.00, 1.39)
Trimethoprim/ Sulfamethoxazole
Sulfamethoxazole | 800 Trimethoprim/ 160 Sulfamethoxazole q12h, 7 days | 400 q6h, 7 days | 12 | 1.01 (0.95, 1.08) | 1.05 (1.01, 1.09) | 1.05 (0.97, 1.14)
Vardenafil | 10 single dose | 800 three times daily | 18 | See text below for discussion of interaction.
Zidovudine | 200 three times daily, 7 days | 1000 three times daily, 7 days | 12 | 0.89 (0.73, 1.09) | 1.17 (1.07, 1.29) | 1.51 (0.71, 3.20) n=4
Zidovudine/ Lamivudine
Zidovudine | 200/150 three times daily, 7 days | 800 three times daily, 7 days | 6, 7 | 1.23 (0.74, 2.03) | 1.39 (1.02, 1.89) | 1.08 (0.77, 1.50) n=5, 5
Zidovudine/ Lamivudine
Lamivudine | 200/150 three times daily, 7 days | 800 three times daily, 7 days | 6, 7 | 0.73 (0.52, 1.02) | 0.91 (0.66, 1.26) | 0.88 (0.59, 1.33)
All interaction studies conducted in healthy, HIV-negative adult subjects, unless otherwise indicated.

Delavirdine: Delavirdine inhibits the metabolism of indinavir such that coadministration of 400-mg or 600-mg indinavir three times daily with 400-mg delavirdine three times daily alters indinavir AUC, Cmax and Cmin (see Table 2). Indinavir had no effect on delavirdine pharmacokinetics (see DOSAGE AND ADMINISTRATION, Concomitant Therapy, Delavirdine), based on a comparison to historical delavirdine pharmacokinetic data.

Methadone: Administration of indinavir (800 mg every 8 hours) with methadone (20 mg to 60 mg daily) for one week in subjects on methadone maintenance resulted in no change in methadone AUC. Based on a comparison to historical data, there was little or no change in indinavir AUC.

Ritonavir: Compared to historical data in patients who received indinavir 800 mg every 8 hours alone, twice-daily coadministration to volunteers of indinavir 800 mg and ritonavir with food for two weeks resulted in a 2.7-fold increase of indinavir AUC24h, a 1.6-fold increase in indinavir Cmax, and an 11-fold increase in indinavir Cmin for a 100-mg ritonavir dose and a 3.6-fold increase of indinavir AUC24h, a 1.8- fold increase in indinavir Cmax, and a 24-fold increase in indinavir Cmin for a 200-mg ritonavir dose. In the same study, twice-daily coadministration of indinavir (800 mg) and ritonavir (100 or 200 mg) resulted in ritonavir AUC24h increases versus the same doses of ritonavir alone (see Table 3).

Sildenafil: The results of one published study in HIV-infected men (n=6) indicated that coadministration of indinavir (800 mg every 8 hours chronically) with a single 25-mg dose of sildenafil resulted in an 11% increase in average AUC0-8hr of indinavir and a 48% increase in average indinavir peak concentration (Cmax) compared to 800 mg every 8 hours alone. Average sildenafil AUC was increased by 340% following coadministration of sildenafil and indinavir compared to historical data following administration of sildenafil alone (see CONTRAINDICATIONS, WARNINGS, Drug Interactions and PRECAUTIONS, Drug Interactions).

Vardenafil: Indinavir (800 mg every 8 hours) coadministered with a single 10-mg dose of vardenafil resulted in a 16-fold increase in vardenafil AUC, a 7-fold increase in vardenafil Cmax, and a 2-fold increase in vardenafil half-life (see WARNINGS, Drug Interactions and PRECAUTIONS, Drug Interactions).

INDICATIONS AND USAGE

CRIXIVAN in combination with antiretroviral agents is indicated for the treatment of HIV infection.

This indication is based on two clinical trials of approximately 1 year duration that demonstrated: 1) a reduction in the risk of AIDS-defining illnesses or death; 2) a prolonged suppression of HIV RNA.

Description of Studies

In all clinical studies, with the exception of ACTG 320, the AMPLICOR HIV MONITOR assay was used to determine the level of circulating HIV RNA in serum. This is an experimental use of the assay. HIV RNA results should not be directly compared to results from other trials using different HIV RNA assays or using other sample sources.

Study ACTG 320 was a multicenter, randomized, double-blind clinical endpoint trial to compare the effect of CRIXIVAN in combination with zidovudine and lamivudine with that of zidovudine plus lamivudine on the progression to an AIDS-defining illness (ADI) or death. Patients were protease inhibitor and lamivudine naive and zidovudine experienced, with CD4 cell counts of ≤200 cells/mm^3. The study enrolled 1156 HIV-infected patients (17% female, 28% Black, 18% Hispanic, mean age 39 years). The mean baseline CD4 cell count was 87 cells/mm^3. The mean baseline HIV RNA was 4.95 log10 copies/mL (89,035 copies/mL). The study was terminated after a planned interim analysis, resulting in a median follow-up of 38 weeks and a maximum follow-up of 52 weeks. Results are shown in Table 4 and Figures 1 & 2.

Table 4: ACTG 320
 |  | Number (%) of Patients with AIDS-defining Illness or Death
Endpoint |  | IDV+ZDV+L (n=577) | ZDV+L (n=579)
HIV Progression or Death |  | 35 (6.1) | 63 (10.9)
Death [The number of deaths is inadequate to assess the impact of Indinavir on survival.] |  | 10 (1.7) | 19 (3.3)
IDV = Indinavir, ZDV = Zidovudine, L = Lamivudine

Study ACTG 320: Figure 1 - Indinavir Protocol ACTG 320 Zidovudine Experienced Plasma Viral RNA - Proportions Below 400 copies/mL
Study ACTG 320: Figure 2 - ACTG 320 Zidovudine Experienced CD4 Cell Counts - Mean Change from Baseline

Study 028, a double-blind, multicenter, randomized, clinical endpoint trial conducted in Brazil, compared the effects of CRIXIVAN plus zidovudine with those of CRIXIVAN alone or zidovudine alone on the progression to an ADI or death, and on surrogate marker responses. All patients were antiretroviral naive with CD4 cell counts of 50 to 250 cells/mm^3. The study enrolled 996 HIV-1 seropositive patients [28% female, 11% Black, 1% Asian/Other, median age 33 years, mean baseline CD4 cell count of 152 cells/mm^3, mean serum viral RNA of 4.44 log10 copies/mL (27,824 copies/mL)]. Treatment regimens containing zidovudine were modified in a blinded manner with the optional addition of lamivudine (median time: week 40). The median length of follow-up was 56 weeks with a maximum of 97 weeks. The study was terminated after a planned interim analysis, resulting in a median follow-up of 56 weeks and a maximum follow-up of 97 weeks. Results are shown in Table 5 and Figures 3 and 4.

Table 5: Protocol 028
 | Number (%) of Patients with AIDS-defining Illness or Death
Endpoint | IDV+ZDV (n=332) | IDV (n=332) | ZDV (n=332)
HIV Progression or Death | 21 (6.3) | 27 (8.1) | 62 (18.7)
Death [The number of deaths is inadequate to assess the impact of Indinavir on survival.] | 8 (2.4) | 5 (1.5) | 11 (3.3)

Study 028: Figure 3 - Indinavir Protocol 028 Zidovudine Naive Viral RNA - Proportions Below 500 Copies/mL in Serum
Study 028: Figure 4 - Indinavir Protocol 028 Zidovudine Naive CD4 Cell Counts - Mean Change from Baseline

Study 035 was a multicenter, randomized trial in 97 HIV-1 seropositive patients who were zidovudine-experienced (median exposure 30 months), protease-inhibitor- and lamivudine-naive, with mean baseline CD4 count 175 cells/mm^3 and mean baseline serum viral RNA 4.62 log10 copies/mL (41,230 copies/mL). Comparisons included CRIXIVAN plus zidovudine plus lamivudine vs. CRIXIVAN alone vs. zidovudine plus lamivudine. After at least 24 weeks of randomized, double-blind therapy, patients were switched to open-label CRIXIVAN plus lamivudine plus zidovudine. Mean changes in log10 viral RNA in serum, the proportions of patients with viral RNA below 500 copies/mL in serum, and mean changes in CD4 cell counts, during 24 weeks of randomized, double-blinded therapy are summarized in Figures 5, 6, and 7, respectively. A limited number of patients remained on randomized, double-blind treatment for longer periods; based on this extended treatment experience, it appears that a greater number of subjects randomized to CRIXIVAN plus zidovudine plus lamivudine demonstrated HIV RNA levels below 500 copies/mL during one year of therapy as compared to those in other treatment groups.

Study 035: Figure 5 - Indinavir Protocol 035 Zidovudine Experienced Viral RNA - Mean Log10 Change from Baseline in Serum
Study 035: Figure 6 - Indinavir Protocol 035 Zidovudine Experienced Viral RNA - Proportions Below 500 Copies/mL in Serum
Study 035: Figure 7 - Indinavir Protocol 035 Zidovudine Experienced CD4 Cell Counts - Mean Change from Baseline

Genotypic Resistance in Clinical Studies

Study 006 (10/15/93-10/12/94) was a dose-ranging study in which patients were initially treated with CRIXIVAN at a dose of <2.4 g/day followed by 2.4 g/day. Study 019 (6/23/94-4/10/95) was a randomized comparison of CRIXIVAN 600 mg every 6 hours, CRIXIVAN plus zidovudine, and zidovudine alone. Table 6 shows the incidence of genotypic resistance at 24 weeks in these studies.

Table 6: Genotypic Resistance at 24 Weeks
Treatment Group | Resistance to IDV n/N [N - includes patients with non-amplifiable virus at 24 weeks who had amplifiable virus at week 0.] | Resistance to ZDV n/N
IDV | — | —
<2.4 g/day | 31/37 (84%) | —
2.4 g/day | 9/21 (43%) | 1/17 (6%)
IDV/ZDV | 4/22 (18%) | 1/22 (5%)
ZDV | 1/18 (6%) | 11/17 (65%)

CONTRAINDICATIONS

CRIXIVAN is contraindicated in patients with clinically significant hypersensitivity to any of its components.

Inhibition of CYP3A4 by CRIXIVAN can result in elevated plasma concentrations of the following drugs, potentially causing serious or life-threatening reactions:

Table 7: Drug Interactions With Crixivan: Contraindicated Drugs
Drug Class | Drugs Within Class That Are Contraindicated With CRIXIVAN
Alpha 1-adrenoreceptor antagonist | alfuzosin
Antiarrhythmics | amiodarone
Ergot derivatives | dihydroergotamine, ergonovine, ergotamine, methylergonovine
GI motility agents | cisapride
HMG-CoA Reductase Inhibitors | lovastatin, simvastatin
Neuroleptics | pimozide
PDE5 Inhibitors | Revatio [Registered trademark of Pfizer, Inc.] (sildenafil) [for treatment of pulmonary arterial hypertension]
Sedative/hypnotics | oral midazolam, triazolam, alprazolam

WARNINGS

ALERT: Find out about medicines that should NOT be taken with CRIXIVAN. This statement is included on the product's bottle label.

Nephrolithiasis/Urolithiasis

Nephrolithiasis/urolithiasis has occurred with CRIXIVAN therapy. The cumulative frequency of nephrolithiasis is substantially higher in pediatric patients (29%) than in adult patients (12.4%; range across individual trials: 4.7% to 34.4%). The cumulative frequency of nephrolithiasis events increases with increasing exposure to CRIXIVAN; however, the risk over time remains relatively constant. In some cases, nephrolithiasis/urolithiasis has been associated with renal insufficiency or acute renal failure, pyelonephritis with or without bacteremia. If signs or symptoms of nephrolithiasis/urolithiasis occur, (including flank pain, with or without hematuria or microscopic hematuria), temporary interruption (e.g., 1-3 days) or discontinuation of therapy may be considered. Adequate hydration is recommended in all patients treated with CRIXIVAN. (See ADVERSE REACTIONS and DOSAGE AND ADMINISTRATION, Nephrolithiasis/Urolithiasis.)

Hemolytic Anemia

Acute hemolytic anemia, including cases resulting in death, has been reported in patients treated with CRIXIVAN. Once a diagnosis is apparent, appropriate measures for the treatment of hemolytic anemia should be instituted, including discontinuation of CRIXIVAN.

Hepatitis

Hepatitis including cases resulting in hepatic failure and death has been reported in patients treated with CRIXIVAN. Because the majority of these patients had confounding medical conditions and/or were receiving concomitant therapy(ies), a causal relationship between CRIXIVAN and these events has not been established.

Hyperglycemia

New onset diabetes mellitus, exacerbation of pre-existing diabetes mellitus and hyperglycemia have been reported during post-marketing surveillance in HIV-infected patients receiving protease inhibitor therapy. Some patients required either initiation or dose adjustments of insulin or oral hypoglycemic agents for treatment of these events. In some cases, diabetic ketoacidosis has occurred. In those patients who discontinued protease inhibitor therapy, hyperglycemia persisted in some cases. Because these events have been reported voluntarily during clinical practice, estimates of frequency cannot be made and a causal relationship between protease inhibitor therapy and these events has not been established.

Drug Interactions

Concomitant use of CRIXIVAN with lovastatin or simvastatin is contraindicated due to an increased risk of myopathy including rhabdomyolysis. Caution should be exercised if CRIXIVAN is used concurrently with atorvastatin or rosuvastatin. Titrate the atorvastatin and rosuvastatin doses carefully and use the lowest necessary dose with CRIXIVAN. (See PRECAUTIONS, Drug Interactions.)

Midazolam is extensively metabolized by CYP3A4. Co-administration with CRIXIVAN with or without ritonavir may cause a large increase in the concentration of this benzodiazepine. No drug interaction study has been performed for the co-administration of CRIXIVAN with benzodiazepines. Based on data from other CYP3A4 inhibitors, plasma concentrations of midazolam are expected to be significantly higher when midazolam is given orally. Therefore CRIXIVAN should not be co-administered with orally administered midazolam (see CONTRAINDICATIONS), whereas caution should be used with co-administration of CRIXIVAN and parenteral midazolam. Data from concomitant use of parenteral midazolam with other protease inhibitors suggest a possible 3-4 fold increase in midazolam plasma levels. If CRIXIVAN with or without ritonavir is co-administered with parenteral midazolam, it should be done in a setting which ensures close clinical monitoring and appropriate medical management in case of respiratory depression and/or prolonged sedation. Dosage reduction for midazolam should be considered, especially if more than a single dose of midazolam is administered.

Particular caution should be used when prescribing sildenafil, tadalafil, or vardenafil in patients receiving indinavir. Coadministration of CRIXIVAN with these medications is expected to substantially increase plasma concentrations of sildenafil, tadalafil, and vardenafil and may result in an increase in adverse events, including hypotension, visual changes, and priapism, which have been associated with sildenafil, tadalafil, and vardenafil (see CONTRAINDICATIONS and PRECAUTIONS, Drug Interactions and Information for Patients, and the manufacturer's complete prescribing information for sildenafil, tadalafil, or vardenafil).

Concomitant use of CRIXIVAN and St. John's wort (Hypericum perforatum) or products containing St. John's wort is not recommended. Coadministration of CRIXIVAN and St. John's wort has been shown to substantially decrease indinavir concentrations (see CLINICAL PHARMACOLOGY, Drug Interactions) and may lead to loss of virologic response and possible resistance to CRIXIVAN or to the class of protease inhibitors.

PRECAUTIONS

General

Indirect hyperbilirubinemia has occurred frequently during treatment with CRIXIVAN and has infrequently been associated with increases in serum transaminases (see also ADVERSE REACTIONS, Clinical Trials and Post-Marketing Experience). It is not known whether CRIXIVAN will exacerbate the physiologic hyperbilirubinemia seen in neonates. (See Pregnancy.)

Tubulointerstitial Nephritis

Reports of tubulointerstitial nephritis with medullary calcification and cortical atrophy have been observed in patients with asymptomatic severe leukocyturia (>100 cells/ high power field). Patients with asymptomatic severe leukocyturia should be followed closely and monitored frequently with urinalyses. Further diagnostic evaluation may be warranted, and discontinuation of CRIXIVAN should be considered in all patients with severe leukocyturia.

Immune reconstitution syndrome has been reported in patients treated with combination antiretroviral therapy, including CRIXIVAN. During the initial phase of combination antiretroviral treatment, patients whose immune system responds may develop an inflammatory response to indolent or residual opportunistic infections (such as Mycobacterium avium infection, cytomegalovirus, Pneumocystis jirovecii pneumonia [PCP], or tuberculosis), which may necessitate further evaluation and treatment.

Autoimmune disorders (such as Graves' disease, polymyositis, and Guillain-Barré syndrome) have also been reported to occur in the setting of immune reconstitution; however, the time to onset is more variable, and can occur many months after initiation of treatment.

Coexisting Conditions

Patients with hemophilia: There have been reports of spontaneous bleeding in patients with hemophilia A and B treated with protease inhibitors. In some patients, additional factor VIII was required. In many of the reported cases, treatment with protease inhibitors was continued or restarted. A causal relationship between protease inhibitor therapy and these episodes has not been established. (See ADVERSE REACTIONS, Post-Marketing Experience.)

Patients with hepatic insufficiency due to cirrhosis: In these patients, the dosage of CRIXIVAN should be lowered because of decreased metabolism of CRIXIVAN (see DOSAGE AND ADMINISTRATION).

Patients with renal insufficiency: Patients with renal insufficiency have not been studied.

Fat Redistribution

Redistribution/accumulation of body fat including central obesity, dorsocervical fat enlargement (buffalo hump), peripheral wasting, facial wasting, breast enlargement, and "cushingoid appearance" have been observed in patients receiving antiretroviral therapy. The mechanism and long-term consequences of these events are currently unknown. A causal relationship has not been established.

Information for Patients

A statement to patients and health care providers is included on the product's bottle label. ALERT: Find out about medicines that should NOT be taken with CRIXIVAN. A Patient Package Insert (PPI) for CRIXIVAN is available for patient information.

CRIXIVAN is not a cure for HIV-1 infection and patients may continue to experience illnesses associated with HIV-1 infection, including opportunistic infections. Patients should remain under the care of a physician when using CRIXIVAN.

Patients should be advised to avoid doing things that can spread HIV-1 infection to others.

- Do not share needles or other injection equipment.
- Do not share personal items that can have blood or body fluids on them, like toothbrushes and razor blades.
- Do not have any kind of sex without protection. Always practice safe sex by using a latex or polyurethane condom to lower the chance of sexual contact with semen, vaginal secretions, or blood.
- Do not breastfeed. We do not know if CRIXIVAN can be passed to your baby in your breast milk and whether it could harm your baby. Also, mothers with HIV-1 should not breastfeed because HIV-1 can be passed to the baby in the breast milk.

Patients should be advised to remain under the care of a physician when using CRIXIVAN and should not modify or discontinue treatment without first consulting the physician. Therefore, if a dose is missed, patients should take the next dose at the regularly scheduled time and should not double this dose. Therapy with CRIXIVAN should be initiated and maintained at the recommended dosage.

CRIXIVAN may interact with some drugs; therefore, patients should be advised to report to their doctor the use of any other prescription, non-prescription medication or herbal products, particularly St. John's wort.

For optimal absorption, CRIXIVAN should be administered without food but with water 1 hour before or 2 hours after a meal. Alternatively, CRIXIVAN may be administered with other liquids such as skim milk, juice, coffee, or tea, or with a light meal, e.g., dry toast with jelly, juice, and coffee with skim milk and sugar; or corn flakes, skim milk and sugar (see CLINICAL PHARMACOLOGY, Effect of Food on Oral Absorption and DOSAGE AND ADMINISTRATION). Ingestion of CRIXIVAN with a meal high in calories, fat, and protein reduces the absorption of indinavir.

Patients receiving a phosphodiesterase type 5 (PDE5) inhibitor (sildenafil, tadalafil, or vardenafil) should be advised that they may be at an increased risk of PDE5 inhibitor-associated adverse events including hypotension, visual changes, and priapism, and should promptly report any symptoms to their doctors (see CONTRAINDICATIONS and WARNINGS, Drug Interactions).

Patients should be informed that redistribution or accumulation of body fat may occur in patients receiving antiretroviral therapy and that the cause and long-term health effects of these conditions are not known at this time.

CRIXIVAN Capsules are sensitive to moisture. Patients should be informed that CRIXIVAN should be stored and used in the original container and the desiccant should remain in the bottle.

Drug Interactions

Indinavir is an inhibitor of the cytochrome P450 isoform CYP3A4. Coadministration of CRIXIVAN and drugs primarily metabolized by CYP3A4 may result in increased plasma concentrations of the other drug, which could increase or prolong its therapeutic and adverse effects (see CONTRAINDICATIONS and WARNINGS).

Indinavir is metabolized by CYP3A4. Drugs that induce CYP3A4 activity would be expected to increase the clearance of indinavir, resulting in lowered plasma concentrations of indinavir. Coadministration of CRIXIVAN and other drugs that inhibit CYP3A4 may decrease the clearance of indinavir and may result in increased plasma concentrations of indinavir.

Table 8: Drugs That Should Not Be Coadministered with CRIXIVAN
Drug Class: Drug Name | Clinical Comment
Alpha 1-adrenoreceptor antagonist: alfuzosin | Potentially increased alfuzosin concentrations can result in hypotension.
Antiarrhythmics: amiodarone | CONTRAINDICATED due to potential for serious and/or life-threatening reactions such as cardiac arrhythmias.
Antimycobacterial: rifampin | May lead to loss of virologic response and possible resistance to CRIXIVAN or to the class of protease inhibitors or other coadministered antiretroviral agents.
Ergot derivatives: dihydroergotamine, ergonovine, ergotamine, methylergonovine | CONTRAINDICATED due to potential for serious and/or life-threatening reactions such as acute ergot toxicity characterized by peripheral vasospasm and ischemia of the extremities and other tissues.
GI motility agents: cisapride | CONTRAINDICATED due to potential for serious and/or life-threatening reactions such as cardiac arrhythmias.
Herbal products: St. John's wort (Hypericum perforatum) | May lead to loss of virologic response and possible resistance to CRIXIVAN or to the class of protease inhibitors.
HMG-CoA Reductase inhibitors: lovastatin, simvastatin | CONTRAINDICATED due to an increased risk for serious reactions such as myopathy including rhabdomyolysis.
Neuroleptic: pimozide | CONTRAINDICATED due to potential for serious and/or life-threatening reactions such as cardiac arrhythmias.
PDE5 inhibitor: Revatio [Registered trademark of Pfizer, Inc.] (sildenafil) [for treatment of pulmonary arterial hypertension] | A safe and effective dose has not been established when used with CRIXIVAN. There is increased potential for sildenafil-associated adverse events (which include visual disturbances, hypotension, prolonged erection, and syncope).
Protease inhibitor: atazanavir | Both CRIXIVAN and atazanavir are associated with indirect (unconjugated) hyperbilirubinemia. Combinations of these drugs have not been studied and coadministration of CRIXIVAN and atazanavir is not recommended.
Sedative/hypnotics: Oral midazolam, triazolam, alprazolam | CONTRAINDICATED due to potential for serious and/or life-threatening reactions such as prolonged or increased sedation or respiratory depression.

Table 9: Established and Other Potentially Significant Drug Interactions: Alteration in Dose or Regimen May Be Recommended Based on Drug Interaction Studies or Predicted Interaction (See also CLINICAL PHARMACOLOGY for magnitude of interaction, WARNINGS and DOSAGE AND ADMINISTRATION.)
Drug Name | Effect | Clinical Comment
HIV Antiviral Agents
Delavirdine | ↑ indinavir concentration | Dose reduction of CRIXIVAN to 600 mg every 8 hours should be considered when taking delavirdine 400 mg three times a day.
Didanosine |  | Indinavir and didanosine formulations containing buffer should be administered at least one hour apart on an empty stomach.
Efavirenz | ↓ indinavir concentration | The optimal dose of indinavir, when given in combination with efavirenz, is not known. Increasing the indinavir dose to 1000 mg every 8 hours does not compensate for the increased indinavir metabolism due to efavirenz.
Nelfinavir | ↑ indinavir concentration | The appropriate doses for this combination, with respect to efficacy and safety, have not been established.
Nevirapine | ↓ indinavir concentration | Indinavir concentrations may be decreased in the presence of nevirapine. The appropriate doses for this combination, with respect to efficacy and safety, have not been established.
Ritonavir | ↑ indinavir concentration ↑ ritonavir concentration | The appropriate doses for this combination, with respect to efficacy and safety, have not been established. Preliminary clinical data suggest that the incidence of nephrolithiasis is higher in patients receiving indinavir in combination with ritonavir than those receiving CRIXIVAN 800 mg q8h.
Saquinavir | ↑ saquinavir concentration | The appropriate doses for this combination, with respect to efficacy and safety, have not been established.
Other Agents
Antiarrhythmics: bepridil, lidocaine(systemic) and quinidine | ↑ antiarrhythmic agents concentration | Caution is warranted and therapeutic concentration monitoring is recommended for antiarrhythmics when coadministered with CRIXIVAN.
Anticonvulsants: carbamazepine, phenobarbital, phenytoin | ↓ indinavir concentration | Use with caution. CRIXIVAN may not be effective due to decreased indinavir concentrations in patients taking these agents concomitantly.
Antidepressant: Trazodone | ↑ trazodone concentration | Concomitant use of trazodone and CRIXIVAN may increase plasma concentrations of trazodone. Adverse events of nausea, dizziness, hypotension and syncope have been observed following coadministration of trazodone and ritonavir. If trazodone is used with a CYP3A4 inhibitor such as CRIXIVAN, the combination should be used with caution and a lower dose of trazodone should be considered.
Anti-gout: Colchicine | ↑ colchicine concentration | Patients with renal or hepatic impairment should not be given colchicine with CRIXIVAN. Treatment of gout flares: Co-administration of colchicine in patients on CRIXIVAN: 0.6 mg (1 tablet) x 1 dose, followed by 0.3 mg (half tablet) 1 hour later. Dose to be repeated no earlier than 3 days. Prophylaxis of gout flares: Co-administration of colchicine in patients on CRIXIVAN: If the original colchicine regimen was 0.6 mg twice a day, the regimen should be adjusted to 0.3 mg once a day. If the original colchicine regimen was 0.6 mg once a day, the regimen should be adjusted to 0.3 mg once every other day. Treatment of familial Mediterranean fever (FMF): Co-administration of colchicine in patients on CRIXIVAN: Maximum daily dose of 0.6 mg (may be given as 0.3 mg twice a day).
Calcium Channel Blockers, Dihydropyridine: e.g., felodipine, nifedipine, nicardipine | ↑ dihydropyridine calcium channel blockers concentration | Caution is warranted and clinical monitoring of patients is recommended.
Clarithromycin | ↑ clarithromycin concentration ↑ indinavir concentration | The appropriate doses for this combination, with respect to efficacy and safety, have not been established.
Endothelin receptor antagonist: Bosentan | ↑ bosentan concentration | Co-administration of bosentan in patients on CRIXIVAN or co-administration of CRIXIVAN in patients on bosentan: Start at or adjust bosentan to 62.5 mg once daily or every other day based upon individual tolerability.
HMG-CoA Reductase Inhibitors: atorvastatin, rosuvastatin | ↑ atorvastatin concentration ↑ rosuvastatin concentration | The atorvastatin and rosuvastatin doses should be carefully titrated; use the lowest dose necessary with careful monitoring during treatment with CRIXIVAN.
Immunosuppressants: cyclosporine, tacrolimus, sirolimus | ↑ immunosuppressant agents concentration | Plasma concentrations may be increased by CRIXIVAN.
Inhaled beta agonist: Salmeterol | ↑ salmeterol | Concurrent administration of salmeterol with CRIXIVAN is not recommended. The combination may result in increased risk of cardiovascular adverse events associated with salmeterol, including QT prolongation, palpitations and sinus tachycardia.
Inhaled/nasal steroid: Fluticasone | ↑ fluticasone concentration | Concomitant use of fluticasone propionate and CRIXIVAN may increase plasma concentrations of fluticasone propionate. Use with caution. Consider alternatives to fluticasone propionate, particularly for long-term use. Fluticasone use is not recommended in situations where CRIXIVAN is coadministered with a potent CYP3A4 inhibitor such as ritonavir unless the potential benefit to the patient outweighs the risk of systemic corticosteroid side effects.
Itraconazole | ↑ indinavir concentration | Dose reduction of CRIXIVAN to 600 mg every 8 hours is recommended when administering itraconazole concurrently.
Ketoconazole | ↑ indinavir concentration | Dose reduction of CRIXIVAN to 600 mg every 8 hours should be considered.
Midazolam (parenteral administration) | ↑ midazolam concentration | Concomitant use of parenteral midazolam with CRIXIVAN may increase plasma concentrations of midazolam. Coadministration should be done in a setting which ensures close clinical monitoring and appropriate medical management in case of respiratory depression and/or prolonged sedation. Dosage reduction for midazolam should be considered, especially if more than a single dose of midazolam is administered. Coadministration of oral midazolam with CRIXIVAN is CONTRAINDICATED (see Table 8).
Rifabutin | ↓ indinavir concentration ↑ rifabutin concentration | Dose reduction of rifabutin to half the standard dose and a dose increase of CRIXIVAN to 1000 mg every 8 hours are recommended when rifabutin and CRIXIVAN are coadministered.
Sildenafil | ↑ sildenafil concentration (only the use of sildenafil at doses used for treatment of erectile dysfunction has been studied with CRIXIVAN) | May result in an increase in PDE5 inhibitor-associated adverse events, including hypotension, syncope, visual disturbances, and priapism. Use of sildenafil for pulmonary arterial hypertension (PAH): Use of Revatio [Registered trademark of Pfizer, Inc.] (sildenafil) is contraindicated when used for the treatment of pulmonary arterial hypertension (PAH) [see CONTRAINDICATIONS]. Use of sildenafil for erectile dysfunction: Sildenafil dose should not exceed a maximum of 25 mg in a 48-hour period in patients receiving concomitant CRIXIVAN therapy. Use with increased monitoring for adverse events.
Tadalafil | ↑ tadalafil concentration | May result in an increase in PDE5 inhibitor-associated adverse events, including hypotension, visual disturbances, and priapism. Use of tadalafil for pulmonary arterial hypertension (PAH): The following dose adjustments are recommended for use of Adcirca [Registered trademark of Eli Lilly and Company.] (tadalafil) with CRIXIVAN: Co-administration of Adcirca in patients on CRIXIVAN or co-administration of CRIXIVAN in patients on Adcirca: Start at or adjust Adcirca to 20 mg once daily. Increase to 40 mg once daily based upon individual tolerability. Use of tadalafil for erectile dysfunction: Tadalafil dose should not exceed a maximum of 10 mg in a 72-hour period in patients receiving concomitant CRIXIVAN therapy. Use with increased monitoring for adverse events.
Vardenafil | ↑ vardenafil concentration | Vardenafil dose should not exceed a maximum of 2.5 mg in a 24-hour period in patients receiving concomitant indinavir therapy.
Venlafaxine | ↓ indinavir concentration | In a study of 9 healthy volunteers, venlafaxine administered under steady-state conditions at 150 mg/day resulted in a 28% decrease in the AUC of a single 800 mg oral dose of indinavir and a 36% decrease in indinavir Cmax. Indinavir did not affect the pharmacokinetics of venlafaxine and ODV. The clinical significance of this finding is unknown.
Note: ↑ = increase; ↓ = decrease

Carcinogenesis, Mutagenesis, Impairment of Fertility

Carcinogenicity studies were conducted in mice and rats. In mice, no increased incidence of any tumor type was observed. The highest dose tested in rats was 640 mg/kg/day; at this dose a statistically significant increased incidence of thyroid adenomas was seen only in male rats. At that dose, daily systemic exposure in rats was approximately 1.3 times higher than daily systemic exposure in humans. No evidence of mutagenicity or genotoxicity was observed in in vitro microbial mutagenesis (Ames) tests, in vitro alkaline elution assays for DNA breakage, in vitro and in vivo chromosomal aberration studies, and in vitro mammalian cell mutagenesis assays. No treatment-related effects on mating, fertility, or embryo survival were seen in female rats and no treatment-related effects on mating performance were seen in male rats at doses providing systemic exposure comparable to or slightly higher than that with the clinical dose. In addition, no treatment-related effects were observed in fecundity or fertility of untreated females mated to treated males.

Pregnancy

Pregnancy Category C:

Developmental toxicity studies were performed in rabbits (at doses up to 240 mg/kg/day), dogs (at doses up to 80 mg/kg/day), and rats (at doses up to 640 mg/kg/day). The highest doses in these studies produced systemic exposures in these species comparable to or slightly greater than human exposure. No treatment-related external, visceral, or skeletal changes were observed in rabbits or dogs. No treatment-related external or visceral changes were observed in rats. Treatment-related increases over controls in the incidence of supernumerary ribs (at exposures at or below those in humans) and of cervical ribs (at exposures comparable to or slightly greater than those in humans) were seen in rats. In all three species, no treatment-related effects on embryonic/fetal survival or fetal weights were observed.

In rabbits, at a maternal dose of 240 mg/kg/day, no drug was detected in fetal plasma 1 hour after dosing. Fetal plasma drug levels 2 hours after dosing were approximately 3% of maternal plasma drug levels. In dogs, at a maternal dose of 80 mg/kg/day, fetal plasma drug levels were approximately 50% of maternal plasma drug levels both 1 and 2 hours after dosing. In rats, at maternal doses of 40 and 640 mg/kg/day, fetal plasma drug levels were approximately 10 to 15% and 10 to 20% of maternal plasma drug levels 1 and 2 hours after dosing, respectively.

Indinavir was administered to Rhesus monkeys during the third trimester of pregnancy (at doses up to 160 mg/kg twice daily) and to neonatal Rhesus monkeys (at doses up to 160 mg/kg twice daily). When administered to neonates, indinavir caused an exacerbation of the transient physiologic hyperbilirubinemia seen in this species after birth; serum bilirubin values were approximately fourfold above controls at 160 mg/kg twice daily. A similar exacerbation did not occur in neonates after in utero exposure to indinavir during the third trimester of pregnancy. In Rhesus monkeys, fetal plasma drug levels were approximately 1 to 2% of maternal plasma drug levels approximately 1 hour after maternal dosing at 40, 80, or 160 mg/kg twice daily.

Hyperbilirubinemia has occurred during treatment with CRIXIVAN (see PRECAUTIONS and ADVERSE REACTIONS). It is unknown whether CRIXIVAN administered to the mother in the perinatal period will exacerbate physiologic hyperbilirubinemia in neonates.

There are no adequate and well-controlled studies in pregnant patients. CRIXIVAN should be used during pregnancy only if the potential benefit justifies the potential risk to the fetus.

A CRIXIVAN dose of 800 mg every 8 hours (with zidovudine 200 mg every 8 hours and lamivudine 150 mg twice a day) has been studied in 16 HIV-infected pregnant patients at 14 to 28 weeks of gestation at enrollment (study PACTG 358). Given the substantially lower antepartum exposures observed and the limited data in this patient population, indinavir use is not recommended in HIV-infected pregnant patients (see CLINICAL PHARMACOLOGY, Pregnant Patients).

Antiretroviral Pregnancy Registry

To monitor maternal-fetal outcomes of pregnant patients exposed to CRIXIVAN, an Antiretroviral Pregnancy Registry has been established. Physicians are encouraged to register patients by calling 1-800-258-4263.

Nursing Mothers

Studies in lactating rats have demonstrated that indinavir is excreted in milk. Although it is not known whether CRIXIVAN is excreted in human milk, there exists the potential for adverse effects from indinavir in nursing infants. Mothers should be instructed to discontinue nursing if they are receiving CRIXIVAN. This is consistent with the recommendation by the U.S. Public Health Service Centers for Disease Control and Prevention that HIV-infected mothers not breast-feed their infants to avoid risking postnatal transmission of HIV.

Pediatric Use

The optimal dosing regimen for use of indinavir in pediatric patients has not been established. A dose of 500 mg/m^2 every eight hours has been studied in uncontrolled studies of 70 children, 3 to 18 years of age. The pharmacokinetic profiles of indinavir at this dose were not comparable to profiles previously observed in adults receiving the recommended dose (see CLINICAL PHARMACOLOGY, Pediatric). Although viral suppression was observed in some of the 32 children who were followed on this regimen through 24 weeks, a substantially higher rate of nephrolithiasis was reported when compared to adult historical data (see WARNINGS, Nephrolithiasis/Urolithiasis). Physicians considering the use of indinavir in pediatric patients without other protease inhibitor options should be aware of the limited data available in this population and the increased risk of nephrolithiasis.

Geriatric Use

Clinical studies of CRIXIVAN did not include sufficient numbers of subjects aged 65 and over to determine whether they respond differently from younger subjects. In general, dose selection for an elderly patient should be cautious, reflecting the greater frequency of decreased hepatic, renal or cardiac function and of concomitant disease or other drug therapy.

ADVERSE REACTIONS

Clinical Trials in Adults

Nephrolithiasis/urolithiasis, including flank pain with or without hematuria (including microscopic hematuria), has been reported in approximately 12.4% (301/2429; range across individual trials: 4.7% to 34.4%) of patients receiving CRIXIVAN at the recommended dose in clinical trials with a median follow-up of 47 weeks (range: 1 day to 242 weeks; 2238 patient-years follow-up). The cumulative frequency of nephrolithiasis events increases with duration of exposure to CRIXIVAN; however, the risk over time remains relatively constant. Of the patients treated with CRIXIVAN who developed nephrolithiasis/urolithiasis in clinical trials during the double-blind phase, 2.8% (7/246) were reported to develop hydronephrosis and 4.5% (11/246) underwent stent placement. Following the acute episode, 4.9% (12/246) of patients discontinued therapy. (See WARNINGS and DOSAGE AND ADMINISTRATION, Nephrolithiasis/Urolithiasis.)

Asymptomatic hyperbilirubinemia (total bilirubin ≥2.5 mg/dL), reported predominantly as elevated indirect bilirubin, has occurred in approximately 14% of patients treated with CRIXIVAN. In <1% this was associated with elevations in ALT or AST.

Hyperbilirubinemia and nephrolithiasis/urolithiasis occurred more frequently at doses exceeding 2.4 g/day compared to doses ≤2.4 g/day.

Clinical adverse experiences reported in ≥2% of patients treated with CRIXIVAN alone, CRIXIVAN in combination with zidovudine or zidovudine plus lamivudine, zidovudine alone, or zidovudine plus lamivudine are presented in Table 10.

Table 10: Clinical Adverse Experiences Reported in ≥2% of Patients
 |  | Study 028 Considered Drug-Related and of Moderate or Severe Intensity |  |  | Study ACTG 320 of Unknown Drug Relationship and of Severe or Life-threatening Intensity
 |  | CRIXIVAN | CRIXIVAN plus Zidovudine | Zidovudine | CRIXIVAN plus Zidovudine plus Lamivudine | Zidovudine plus Lamivudine
Adverse Experience |  | Percent (n=332) | Percent (n=332) | Percent (n=332) | Percent (n=571) | Percent (n=575)
Body as a Whole
Abdominal pain |  | 16.6 | 16.0 | 12.0 | 1.9 | 0.7
Asthenia/fatigue |  | 2.1 | 4.2 | 3.6 | 2.4 | 4.5
Fever |  | 1.5 | 1.5 | 2.1 | 3.8 | 3.0
Malaise |  | 2.1 | 2.7 | 1.8 | 0 | 0
Digestive System
Nausea |  | 11.7 | 31.9 | 19.6 | 2.8 | 1.4
Diarrhea |  | 3.3 | 3.0 | 2.4 | 0.9 | 1.2
Vomiting |  | 8.4 | 17.8 | 9.0 | 1.4 | 1.4
Acid regurgitation |  | 2.7 | 5.4 | 1.8 | 0.4 | 0
Anorexia |  | 2.7 | 5.4 | 3.0 | 0.5 | 0.2
Appetite increase |  | 2.1 | 1.5 | 1.2 | 0 | 0
Dyspepsia |  | 1.5 | 2.7 | 0.9 | 0 | 0
Jaundice |  | 1.5 | 2.1 | 0.3 | 0 | 0
Hemic and Lymphatic System
Anemia |  | 0.6 | 1.2 | 2.1 | 2.4 | 3.5
Musculoskeletal System
Back pain |  | 8.4 | 4.5 | 1.5 | 0.9 | 0.7
Nervous System/Psychiatric
Headache |  | 5.4 | 9.6 | 6.0 | 2.4 | 2.8
Dizziness |  | 3.0 | 3.9 | 0.9 | 0.5 | 0.7
Somnolence |  | 2.4 | 3.3 | 3.3 | 0 | 0
Skin and Skin Appendage
Pruritus |  | 4.2 | 2.4 | 1.8 | 0.5 | 0
Rash |  | 1.2 | 0.6 | 2.4 | 1.1 | 0.5
Respiratory System
Cough |  | 1.5 | 0.3 | 0.6 | 1.6 | 1.0
Difficulty breathing/ dyspnea/ shortness of breath |  | 0 | 0.6 | 0.3 | 1.8 | 1.0
Urogenital System
Nephrolithiasis/urolithiasis [Including renal colic, and flank pain with and without hematuria] |  | 8.7 | 7.8 | 2.1 | 2.6 | 0.3
Dysuria |  | 1.5 | 2.4 | 0.3 | 0.4 | 0.2
Special Senses
Taste perversion |  | 2.7 | 8.4 | 1.2 | 0.2 | 0

In Phase I and II controlled trials, the following adverse events were reported significantly more frequently by those randomized to the arms containing CRIXIVAN than by those randomized to nucleoside analogues: rash, upper respiratory infection, dry skin, pharyngitis, taste perversion.

Selected laboratory abnormalities of severe or life-threatening intensity reported in patients treated with CRIXIVAN alone, CRIXIVAN in combination with zidovudine or zidovudine plus lamivudine, zidovudine alone, or zidovudine plus lamivudine are presented in Table 11.

Table 11: Selected Laboratory Abnormalities of Severe or Life-threatening IntensityReported in Studies 028 and ACTG 320
 | Study 028 |  |  | Study ACTG 320
 | CRIXIVAN | CRIXIVAN plus Zidovudine | Zidovudine | CRIXIVAN plus Zidovudine plus Lamivudine | Zidovudine plus Lamivudine
 | Percent (n=329) | Percent (n=320) | Percent (n=330) | Percent (n=571) | Percent (n=575)
Hematology
Decreased hemoglobin <7.0 g/dL | 0.6 | 0.9 | 3.3 | 2.4 | 3.5
Decreased platelet count <50 THS/mm^3 | 0.9 | 0.9 | 1.8 | 0.2 | 0.9
Decreased neutrophils <0.75 THS/mm^3 | 2.4 | 2.2 | 6.7 | 5.1 | 14.6
Blood chemistry
Increased ALT >500% ULN [Upper limit of the normal range.] | 4.9 | 4.1 | 3.0 | 2.6 | 2.6
Increased AST >500% ULN | 3.7 | 2.8 | 2.7 | 3.3 | 2.8
Total serum bilirubin >250% ULN | 11.9 | 9.7 | 0.6 | 6.1 | 1.4
Increased serum amylase >200% ULN | 2.1 | 1.9 | 1.8 | 0.9 | 0.3
Increased glucose >250 mg/dL | 0.9 | 0.9 | 0.6 | 1.6 | 1.9
Increased creatinine >300% ULN | 0 | 0 | 0.6 | 0.2 | 0

Post-Marketing Experience

Body As A Whole: redistribution/accumulation of body fat (see PRECAUTIONS, Fat Redistribution).

Cardiovascular System: cardiovascular disorders including myocardial infarction and angina pectoris; cerebrovascular disorder.

Digestive System: liver function abnormalities; hepatitis including reports of hepatic failure (see WARNINGS); pancreatitis; jaundice; abdominal distention; dyspepsia.

Hematologic: increased spontaneous bleeding in patients with hemophilia (see PRECAUTIONS); acute hemolytic anemia (see WARNINGS).

Endocrine/Metabolic: new onset diabetes mellitus, exacerbation of pre-existing diabetes mellitus, hyperglycemia (see WARNINGS).

Hypersensitivity: anaphylactoid reactions; urticaria; vasculitis.

Musculoskeletal System: arthralgia.

Nervous System/Psychiatric: oral paresthesia; depression.

Skin and Skin Appendage: rash including erythema multiforme and Stevens-Johnson syndrome; hyperpigmentation; alopecia; ingrown toenails and/or paronychia; pruritus.

Urogenital System: nephrolithiasis/urolithiasis, in some cases resulting in renal insufficiency or acute renal failure, pyelonephritis with or without bacteremia (see WARNINGS); interstitial nephritis sometimes with indinavir crystal deposits; in some patients, the interstitial nephritis did not resolve following discontinuation of CRIXIVAN; renal insufficiency; renal failure; leukocyturia (see PRECAUTIONS), crystalluria; dysuria.

Laboratory Abnormalities

Increased serum triglycerides; increased serum cholesterol.

OVERDOSAGE

There have been more than 60 reports of acute or chronic human overdosage (up to 23 times the recommended total daily dose of 2400 mg) with CRIXIVAN. The most commonly reported symptoms were renal (e.g., nephrolithiasis/urolithiasis, flank pain, hematuria) and gastrointestinal (e.g., nausea, vomiting, diarrhea).

It is not known whether CRIXIVAN is dialyzable by peritoneal or hemodialysis.

DOSAGE AND ADMINISTRATION

The recommended dosage of CRIXIVAN is 800 mg (usually two 400-mg capsules) orally every 8 hours.

CRIXIVAN must be taken at intervals of 8 hours. For optimal absorption, CRIXIVAN should be administered without food but with water 1 hour before or 2 hours after a meal. Alternatively, CRIXIVAN may be administered with other liquids such as skim milk, juice, coffee, or tea, or with a light meal, e.g., dry toast with jelly, juice, and coffee with skim milk and sugar; or corn flakes, skim milk and sugar. (See CLINICAL PHARMACOLOGY, Effect of Food on Oral Absorption.)

To ensure adequate hydration, it is recommended that adults drink at least 1.5 liters (approximately 48 ounces) of liquids during the course of 24 hours.

Concomitant Therapy

(See CLINICAL PHARMACOLOGY, Drug Interactions, and/or PRECAUTIONS, Drug Interactions.)

Delavirdine

Dose reduction of CRIXIVAN to 600 mg every 8 hours should be considered when administering delavirdine 400 mg three times a day.

Didanosine

If indinavir and didanosine are administered concomitantly, they should be administered at least one hour apart on an empty stomach (consult the manufacturer's product circular for didanosine).

Itraconazole

Dose reduction of CRIXIVAN to 600 mg every 8 hours is recommended when administering itraconazole 200 mg twice daily concurrently.

Ketoconazole

Dose reduction of CRIXIVAN to 600 mg every 8 hours is recommended when administering ketoconazole concurrently.

Rifabutin

Dose reduction of rifabutin to half the standard dose (consult the manufacturer's product circular for rifabutin) and a dose increase of CRIXIVAN to 1000 mg every 8 hours are recommended when rifabutin and CRIXIVAN are coadministered.

Hepatic Insufficiency

The dosage of CRIXIVAN should be reduced to 600 mg every 8 hours in patients with mild-to-moderate hepatic insufficiency due to cirrhosis.

Nephrolithiasis/Urolithiasis

In addition to adequate hydration, medical management in patients who experience nephrolithiasis/urolithiasis may include temporary interruption (e.g., 1 to 3 days) or discontinuation of therapy.

HOW SUPPLIED

CRIXIVAN Capsules are supplied as follows:

400 mg capsules: semi-translucent white capsules coded "CRIXIVAN™ 400 mg" in green.
Available in bottles of 90: NDC 16590-064-90
Relabeling and Repackaging by:
STAT Rx USA LLC
Gainesville, GA 30501

Storage

Bottles: Store in a tightly-closed container at room temperature, 15-30°C (59-86°F). Protect from moisture.

CRIXIVAN Capsules are sensitive to moisture. CRIXIVAN should be dispensed and stored in the original container. The desiccant should remain in the original bottle.

Dist. by: Merck Sharp & Dohme Corp., a subsidiary of
MERCK & CO., INC., Whitehouse Station, NJ 08889, USA

U.S. Patent Nos.: 6,645,961

Copyright © 1996, 1997, 1998, 1999, 2004 Merck Sharp & Dohme Corp., a subsidiary of Merck & Co., Inc.
All rights reserved.

Issued April 2012

9640615

PATIENT INFORMATION

CRIXIVAN® (indinavir sulfate) Capsules
Patient Information about
CRIXIVAN (KRIK-sih-van)
for HIV (Human Immunodeficiency Virus) Infection
Generic name: indinavir (in-DIH-nuh-veer) sulfate

ALERT: Find out about medicines that should NOT be taken with CRIXIVAN®. Please also read the section "MEDICINES YOU SHOULD NOT TAKE WITH CRIXIVAN".

Please read this information before you start taking CRIXIVAN. Also, read the leaflet each time you renew your prescription, just in case anything has changed. Remember, this leaflet does not take the place of careful discussions with your doctor. You and your doctor should discuss CRIXIVAN when you start taking your medication and at regular checkups. You should remain under a doctor's care when using CRIXIVAN and should not change or stop treatment without first talking with your doctor.

What is CRIXIVAN?

CRIXIVAN is an oral capsule used for the treatment of HIV (Human Immunodeficiency Virus). HIV is the virus that causes AIDS (acquired immune deficiency syndrome). CRIXIVAN is a type of HIV drug called a protease (PRO-tee-ase) inhibitor.

How does CRIXIVAN work?

CRIXIVAN is a protease inhibitor that fights HIV. CRIXIVAN can help reduce your chances of getting illnesses associated with HIV. CRIXIVAN can also help lower the amount of HIV in your body (called "viral load") and raise your CD4 (T) cell count. CRIXIVAN may not have these effects in all patients.

CRIXIVAN is usually prescribed with other anti-HIV drugs such as ZDV (also called AZT), 3TC, ddI, ddC, or d4T. CRIXIVAN works differently from these other anti-HIV drugs. Talk with your doctor about how you should take CRIXIVAN.

How should I take CRIXIVAN?

There are six important things you must do to help you benefit from CRIXIVAN:

1. Take CRIXIVAN capsules every day as prescribed by your doctor. Continue taking CRIXIVAN unless your doctor tells you to stop. Take the exact amount of CRIXIVAN that your doctor tells you to take, right from the very start. To help make sure you will benefit from CRIXIVAN, you must not skip doses or take "drug holidays". If you don't take CRIXIVAN as prescribed, the activity of CRIXIVAN may be reduced (due to resistance).
2. Take CRIXIVAN capsules every 8 hours around the clock, every day. It may be easier to remember to take CRIXIVAN if you take it at the same time every day. If you have questions about when to take CRIXIVAN, your doctor or health care provider can help you decide what schedule works for you.
3. If you miss a dose by more than 2 hours, wait and then take the next dose at the regularly scheduled time. However, if you miss a dose by less than 2 hours, take your missed dose immediately. Then take your next dose at the regularly scheduled time. Do not take more or less than your prescribed dose of CRIXIVAN at any one time.
4. Take CRIXIVAN with water. You can also take CRIXIVAN with other beverages such as skim or non-fat milk, juice, coffee, or tea.
5. Ideally, take each dose of CRIXIVAN without food but with water at least one hour before or two hours after a meal. Or you can take CRIXIVAN with a light meal. Examples of light meals include:
  dry toast with jelly, juice, and coffee (with skim or non-fat milk and sugar if you want)
  cornflakes with skim or non-fat milk and sugar
  Do not take CRIXIVAN at the same time as any meals that are high in calories, fat, and protein (for example — a bacon and egg breakfast). When taken at the same time as CRIXIVAN, these foods can interfere with CRIXIVAN being absorbed into your bloodstream and may lessen its effect.
6. It is critical to drink plenty of fluids while taking CRIXIVAN. Adults should drink at least six 8-ounce glasses of liquids (preferably water) throughout the day, every day. Your health care provider will give you further instructions on the amount of fluid that you should drink. CRIXIVAN can cause kidney stones. Having enough fluids in your body should help reduce the chances of forming a kidney stone. Call your doctor or other health care provider if you develop kidney pains (middle to lower stomach or back pain) or blood in the urine.

Does CRIXIVAN cure HIV or AIDS?

CRIXIVAN does not cure HIV infection or AIDS and you may continue to experience illnesses associated with HIV-1 infection, including opportunistic infections. You should remain under the care of a doctor when using CRIXIVAN.

Avoid doing things that can spread HIV-1 infection.

- Do not share needles or other injection equipment.
- Do not share personal items that can have blood or body fluids on them, like toothbrushes and razor blades.
- Do not have any kind of sex without protection. Always practice safe sex by using a latex or polyurethane condom to lower the chance of sexual contact with semen, vaginal secretions, or blood.

Who should not take CRIXIVAN?

Do not take CRIXIVAN if you have had a serious allergic reaction to CRIXIVAN or any of its components.

What other medical problems or conditions should I discuss with my doctor?

Talk to your doctor if:

- You are pregnant or if you become pregnant while you are taking CRIXIVAN. We do not yet know how CRIXIVAN affects pregnant women or their developing babies.
- You are breastfeeding. Do not breastfeed. We do not know if CRIXIVAN can be passed to your baby in your breast milk and whether it could harm your baby. Also, mothers with HIV-1 should not breastfeed because HIV-1 can be passed to the baby in the breast milk.

Also talk to your doctor if you have:

- Problems with your liver, especially if you have mild or moderate liver disease caused by cirrhosis
- Problems with your kidneys
- Diabetes
- Hemophilia
- High cholesterol and you are taking cholesterol-lowering medicines called "statins"

Tell your doctor about any medicines you are taking or plan to take, including non-prescription medicines, herbal products including St. John's wort (Hypericum perforatum), or dietary supplements.

Can CRIXIVAN be taken with other medications?

MEDICINES YOU SHOULD NOT TAKE WITH CRIXIVAN

Oral VERSED® (midazolam) | HALCION® (triazolam)
ORAP® (pimozide) | XANAX® (alprazolam)
PROPULSID® (cisapride) | REVATIO® (sildenafil for the treatment of pulmonary arterial hypertension)
CORDARONE® (amiodarone) | UROXATRAL® (alfuzosin)
HISMANAL® (astemizole) | Ergot medications (e.g., Wigraine®, Cafergot®, D.H.E. 45®, Migranal®, Ergotrate®, and Methergine®)
 | ZOCOR® (simvastatin) MEVACOR® (lovastatin)

Taking CRIXIVAN with the above medications could result in serious or life-threatening problems (such as irregular heartbeat or excessive sleepiness).

In addition, you should not take CRIXIVAN with the following:

Rifampin, known as RIFADIN®, RIFAMATE®, RIFATER®, or RIMACTANE®.
There is also an increased risk of drug interactions between CRIXIVAN and LIPITOR® (atorvastatin) and CRESTOR® (rosuvastatin); talk to your doctor before you take any of these cholesterol-reducing drugs with CRIXIVAN.
Taking CRIXIVAN with REYATAZ® (atazanavir) is not recommended because they can both sometimes cause increased levels of bilirubin in the blood.
Taking CRIXIVAN with St. John's wort (Hypericum perforatum), an herbal product sold as a dietary supplement, or products containing St. John's wort is not recommended. Taking St. John's wort has been shown to decrease CRIXIVAN levels and may lead to increased viral load and possible resistance to CRIXIVAN or cross resistance to other antiretroviral drugs.

Before you take VIAGRA® (sildenafil), CIALIS® (tadalafil), or LEVITRA® (vardenafil) with CRIXIVAN, talk to your doctor about possible drug interactions and side effects. If you take any of these medicines together with CRIXIVAN, you may be at increased risk of side effects such as low blood pressure, visual changes, and penile erection lasting more than 4 hours, which have been associated with sildenafil, tadalafil, and vardenafil. If an erection lasts longer than 4 hours, you should seek immediate medical assistance to avoid permanent damage to your penis. Your doctor can explain these symptoms to you.

MEDICINES YOU CAN TAKE WITH CRIXIVAN

RETROVIR®
(zidovudine, ZDV also called AZT)

EPIVIR™
(lamivudine, 3TC)

ZERIT®
(stavudine, d4T)

isoniazid
(INH)

BACTRIM®/SEPTRA®
(trimethoprim/sulfamethoxazole)

DIFLUCAN®
(fluconazole)

BIAXIN®
(clarithromycin)

ORTHO-NOVUM 1/35®
(oral contraceptive)

TAGAMET®
(cimetidine)

Methadone

VIDEX® (didanosine, ddI) — If you take CRIXIVAN with VIDEX, take them at least one hour apart.

MYCOBUTIN® (rifabutin) — If you take CRIXIVAN with MYCOBUTIN, your doctor may adjust both the dose of MYCOBUTIN and the dose of CRIXIVAN.

NIZORAL® (ketoconazole) — If you take CRIXIVAN with NIZORAL, your doctor may adjust the dose of CRIXIVAN.

RESCRIPTOR® (delavirdine) — If you take CRIXIVAN with RESCRIPTOR, your doctor may adjust the dose of CRIXIVAN.

SPORANOX® (itraconazole) — If you take CRIXIVAN with SPORANOX, your doctor may adjust the dose of CRIXIVAN.

SUSTIVA™ (efavirenz) — If you take CRIXIVAN with SUSTIVA, check with your doctor.

Intravenous VERSED® (midazolam) — If you take CRIXIVAN with Intravenous VERSED®, your doctor may adjust the dose of VERSED®.

Talk to your doctor about any medications you are taking.

Calcium Channel Blockers: Tell your doctor if you are taking calcium channel blockers (e.g., amlodipine, felodipine).

Antiarrhythmics: Tell your doctor if you are taking antiarrhythmics (e.g., quinidine).

Anticonvulsants: Tell your doctor if you are taking anticonvulsants (e.g., phenobarbital, phenytoin, or carbamazepine).

Steroids: Tell your doctor if you are taking steroids (e.g., dexamethasone).

What are the possible side effects of CRIXIVAN?

Like all prescription drugs, CRIXIVAN can cause side effects. The following is not a complete list of side effects reported with CRIXIVAN when taken either alone or with other anti-HIV drugs. Do not rely on this leaflet alone for information about side effects. Your doctor can discuss with you a more complete list of side effects.

Some patients treated with CRIXIVAN developed kidney stones. In some of these patients this led to more severe kidney problems, including kidney failure or inflammation of the kidneys or kidney infection which sometimes spread to the blood. Drinking at least six 8-ounce glasses of liquids (preferably water) each day should help reduce the chances of forming a kidney stone (see How should I take CRIXIVAN?). Call your doctor or other health care provider if you develop kidney pains (middle to lower stomach or back pain) or blood in the urine.

Some patients treated with CRIXIVAN have had rapid breakdown of red blood cells (hemolytic anemia) which in some cases was severe or resulted in death.

Some patients treated with CRIXIVAN have had liver problems including liver failure and death. Some patients had other illnesses or were taking other drugs. It is uncertain if CRIXIVAN caused these liver problems.

Diabetes and high blood sugar (hyperglycemia) have occurred in patients taking protease inhibitors. In some of these patients, this led to ketoacidosis, a serious condition caused by poorly controlled blood sugar. Some patients had diabetes before starting protease inhibitors, others did not. Some patients required adjustments to their diabetes medication. Others needed new diabetes medication.

In some patients with hemophilia, increased bleeding has been reported.

Severe muscle pain and weakness have occurred in patients taking protease inhibitors, including CRIXIVAN, together with some of the cholesterol-lowering medicines called "statins". Call your doctor if you develop severe muscle pain or weakness.

Changes in body fat have been seen in some patients taking antiretroviral therapy. These changes may include increased amount of fat in the upper back and neck ("buffalo hump"), breast, and around the trunk. Loss of fat from the legs, arms and face may also happen. The cause and long term health effects of these conditions are not known at this time.

In some patients with advanced HIV infection (AIDS), signs and symptoms of inflammation from opportunistic infections may occur when combination antiretroviral treatment is started.

Clinical Studies

Increases in bilirubin (one laboratory test of liver function) have been reported in approximately 14% of patients. Usually, this finding has not been associated with liver problems. However, on rare occasions, a person may develop yellowing of the skin and/or eyes.

Side effects occurring in 2% or more of patients included: abdominal pain, fatigue or weakness, low red blood cell count, flank pain, painful urination, feeling unwell, nausea, upset stomach, diarrhea, vomiting, acid regurgitation, increased or decreased appetite, back pain, headache, dizziness, taste changes, rash, itchy skin, yellowing of the skin and/or eyes, upper respiratory infection, dry skin, and sore throat.

Swollen kidneys due to blocked urine flow occurred rarely.

Marketing Experience

Other side effects reported since CRIXIVAN has been marketed include: allergic reactions; severe skin reactions; yellowing of the skin and/or eyes; heart problems including heart attack; stroke; abdominal swelling; indigestion; inflammation of the kidneys; decreased kidney function; inflammation of the pancreas; joint pain; depression; itching; hives; change in skin color; hair loss; ingrown toenails with or without infection; crystals in the urine; painful urination; numbness of the mouth and increased cholesterol.

Tell your doctor promptly about these or any other unusual symptoms. If the condition persists or worsens, seek medical attention.

How should I store CRIXIVAN capsules?

- Keep CRIXIVAN capsules in the bottle they came in and at room temperature (59°-86°F).
- Keep CRIXIVAN capsules dry by leaving the small desiccant in the bottle. Keep the bottle closed.

This medication was prescribed for your particular condition. Do not use it for any other condition or give it to anybody else. Keep CRIXIVAN and all medicines out of the reach of children. If you suspect that more than the prescribed dose of this medicine has been taken, contact your local poison control center or emergency room immediately.

This leaflet provides a summary of information about CRIXIVAN. If you have any questions or concerns about either CRIXIVAN or HIV, talk to your doctor.

Distributed by:
Merck Sharp & Dohme Corp., a subsidiary of Merck & Co., Inc.
Whitehouse Station, NJ 08889, USA

U.S. Patent Nos.: 6,645,961

The trademarks depicted herein are owned by their respective companies.

Copyright © 1996, 1999 Merck Sharp & Dohme Corp., a subsidiary of Merck & Co., Inc.
All rights reserved

Issued April 2012

9640615

PACKAGE LABEL - CRIXIVAN 400 mg CAPSULES

Crixivan® (Indinavir Sulfate) Capsules 400 mg

Each capsule contains indinavir 400 mg (corresponding to indinavir sulfate 500 mg).

Store at room temperature, 15-30°C (59-86°F).Keep container tightly closed. Protect from moisture.

Rx only